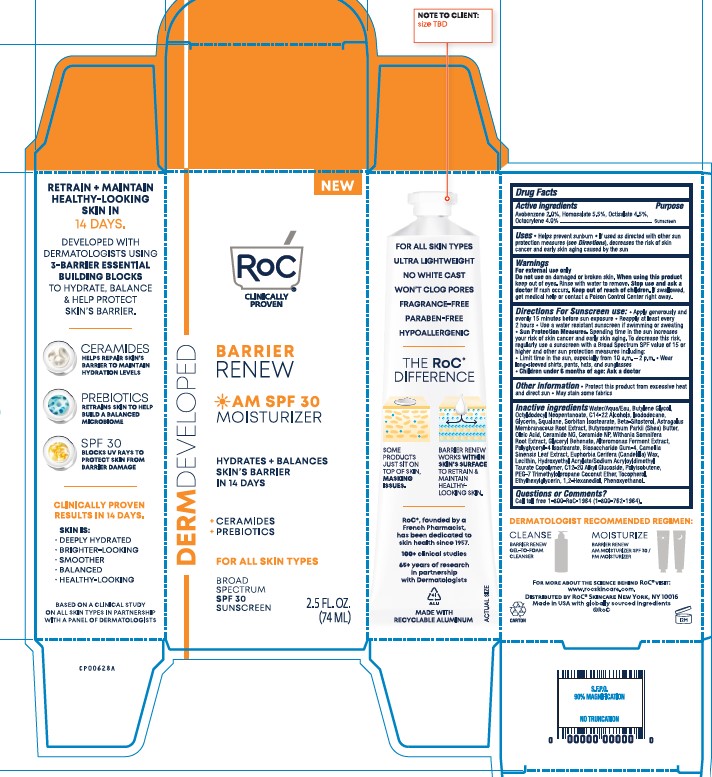 DRUG LABEL: RoC Barrier Renew AM Moisturizer SPF 30
NDC: 73496-011 | Form: LOTION
Manufacturer: RoC Skincare
Category: otc | Type: HUMAN OTC DRUG LABEL
Date: 20251201

ACTIVE INGREDIENTS: AVOBENZONE 2 g/100 mL; OCTOCRYLENE 4 g/100 mL; HOMOSALATE 5.5 g/100 mL; OCTISALATE 4.5 g/100 mL
INACTIVE INGREDIENTS: SHEA BUTTER; WITHANIA SOMNIFERA ROOT; BIOSACCHARIDE GUM-4; CANDELILLA WAX; BUTYLENE GLYCOL; ASTRAGALUS MONGHOLICUS ROOT; OLEIC ACID; 1,2-HEXANEDIOL; TOCOPHEROL; ISODODECANE; GLYCERIN; POLYGLYCERYL-4 ISOSTEARATE; C12-20 ALKYL GLUCOSIDE; ETHYLHEXYLGLYCERIN; GLYCERYL MONOBEHENATE; WATER; C14-22 ALCOHOLS; GREEN TEA LEAF; PEG-7 TRIMETHYLOLPROPANE COCONUT ETHER; PHENOXYETHANOL; SQUALANE; OCTYLDODECYL NEOPENTANOATE; SORBITAN ISOSTEARATE; .BETA.-SITOSTEROL; CERAMIDE NG; CERAMIDE NP

RoC Barrier Renew AM Moisturizer SPF 30

Active Ingredients

Active ingredients Purpose

Avobenzone 2.0%, Homosalate 5.5%, Octisalate 4.5%, Octocrylene 4.0% Sunscreen

Uses

Uses Helps prevent sunburn. If used as directed with other sun protection measures (see Directions), decreases the risk of skin cancer and early signs of aging caused by the sun

Indications and Usage

Helps prevent sunburn. If used as directed with other sun protection measures (see Directions), decreases the risk of skin cancer and early skin aging caused by the sun

Warnings

For external use only

Do nut use on damaged or broken skin. When using this product keep out of eyes. Rinse with water to remove. Stop use and ask a doctor if rash occurs. Keep out of reach of children. If swallowed, get medical help or contact a Poison Control Center right away.

Keep out of reach of children

Directions For Sunscreen use: Apply generously and evenly 15 minutes before sun exposure. Reapply at least every 2 hours. Use a water resistant sunscreen if swimming or sweating. Sun Protection Measures. Spending time in the sun increases your risk of skin cancer and early skin aging. To decrease this risk, regularly use a sunscreen with a Broad Spectrum SPF value of 15 or higher and other sun protection measures including: Limit time in the sun, especially from 10 a.m. - 2 p.m. Wear long-sleeved shirts, pants, hats, and sunglasses. Children under 6 months of age: Ask a doctor.

Other Information

Other information. Protect this product from excessive heat and direct sun. May stain some fabrics.

Inactive Ingredients

Inactive ingredients Water/Aqua/Eau, Butylene Glycol, Octyldodecyl Neopentanoate, C14-22 Alcohols, Isododecane, Glycerin, Squalane, Sorbitan Isostearate, Beta-Sitosterol, Astragalus Membranaceus Root Extract, Butyrospermum Parkii (Shea) Butter, Oleic Acid, Ceramide NG, Ceramide NP, Withania Somnifera Root Extract, Glyceryl Behenate, Alteromonas Ferment Extract, Polyglyceryl-4 Isostearate, Biosaccharide Gum-4, Camellia Sinensis Leaf Extract, Euphorbia Cerifera (Candelilla) Wax, Lecithin, Hydroxyethyl Acrylate/Sodium Acryloyldimethyl Taurate Copolymer, C12-20 Alkyl Glucoside, Polyisobutene, PEG-7 Trimethylolpropane Coconut Ether, Tocopherol, Ethylhexylglycerin, 1,2-Hexanediol, Phenoxyethanol.

Questions or comments?

Call toll free 1-800-RoC-1964 (1-800-762-1964).